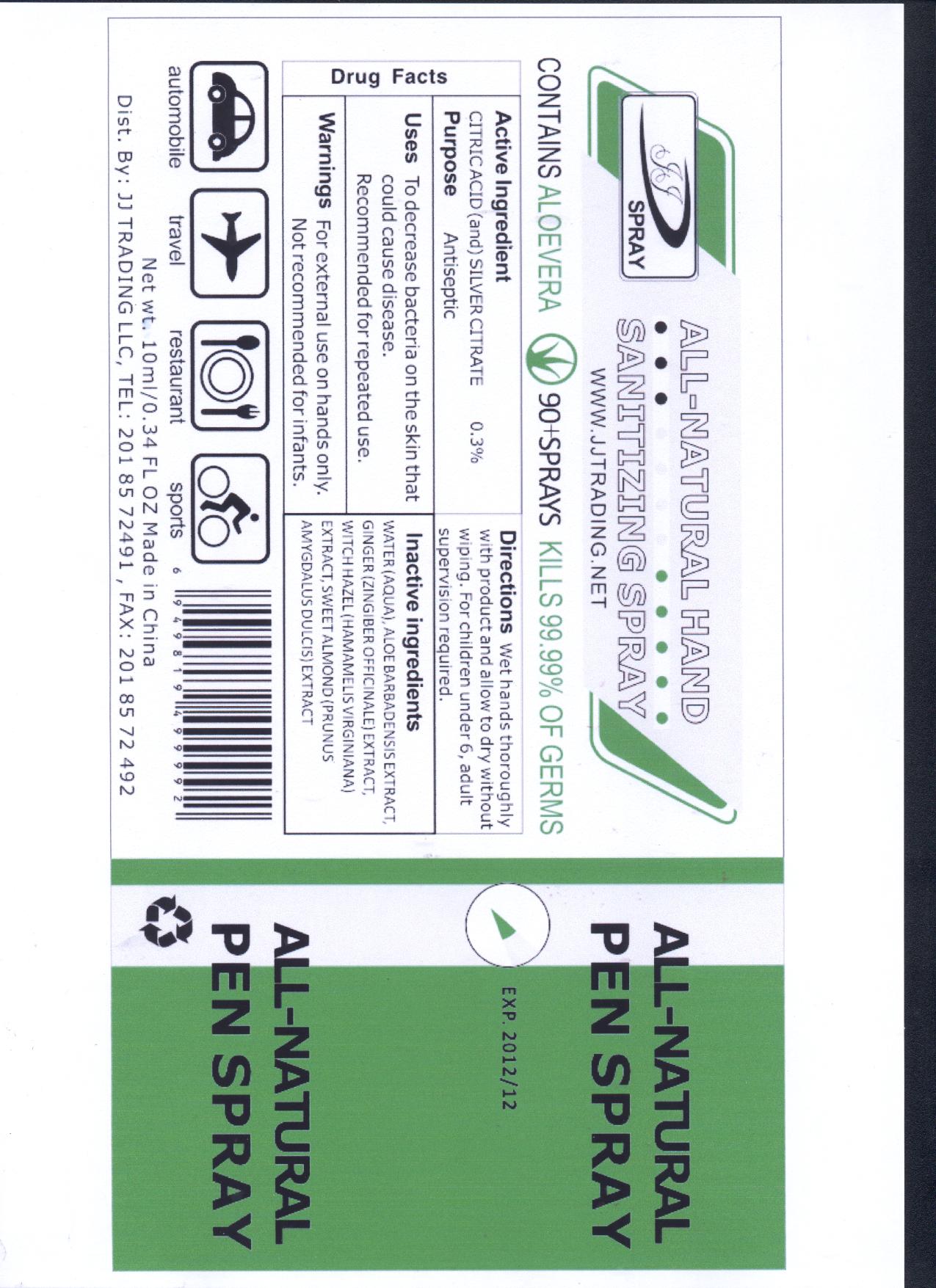 DRUG LABEL: All-Natural Pen Spray
NDC: 50538-001 | Form: AEROSOL, SPRAY
Manufacturer: HANGZHOU KARIC COMMODITIES CO., LTD.
Category: otc | Type: HUMAN OTC DRUG LABEL
Date: 20100203

ACTIVE INGREDIENTS: SILVER CITRATE 0.15 g/100 g; ANHYDROUS CITRIC ACID 0.15 g/100 g
INACTIVE INGREDIENTS: ALOE VERA LEAF 3 g/100 g; WATER 91.7 g/100 g; GINGER 1 g/100 g; WITCH HAZEL 1 g/100 g; ALMOND 3 g/100 g

ALL Natural Hand Sanitizing Spray

Active Ingredient

Active Ingredient: Citric Acid and Silver Citrate 0.3%

Purpose

Purpose: Antiseptic

Uses

Uses: To decrease bacteria on the skin that can cause disease. Recommend for repeated use.

Warnings

Warnings: For external use on hands only. Not recommended for infants.

Directions

Directions: Wet hands thoroughly with product and allow to dry without wiping. For children under 6, adult supervision required.

Inactive Ingredients

Water (aqua), Aloe Barbadensis Extract, Ginger (Zinginber Officinale) Extract, Witch Hazel (Hamamelis Virginiana) Extract, Sweet Almond (Prunus Amygdalus Dulcis) Extract

label